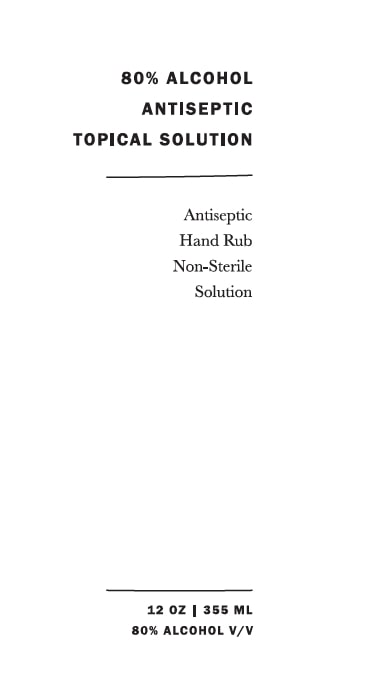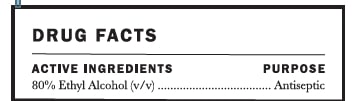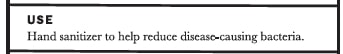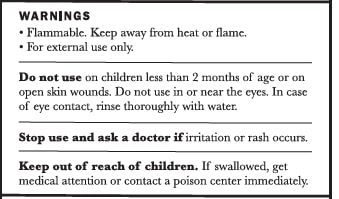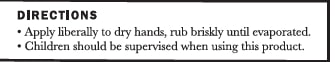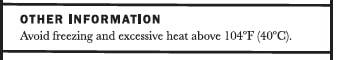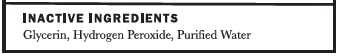 DRUG LABEL: Hand Sanitizer WHO Formulation
NDC: 77419-0002 | Form: LIQUID
Manufacturer: AMASS Brands, Inc
Category: otc | Type: HUMAN OTC DRUG LABEL
Date: 20200611

ACTIVE INGREDIENTS: ALCOHOL 80 mL/100 mL
INACTIVE INGREDIENTS: GLYCERIN 1.45 mL/100 mL; HYDROGEN PEROXIDE 0.125 mL/100 mL; WATER

Active Ingredients

80% Ethyl Alcohol (v/v); Purpose: Antiseptic

Use

Hand sanitizer to help reduce disease-causing bacteria.

Warnings

Flammable. Keep away from heat or flame. For external use only.

Do not use

- on children less than 2 months of age or on open skin wounds. Do not use in or near the eyes. in case of eye contact, rinse thoroughly with water.

Stop use and ask a doctor if irritation or rash occurs.

Stop use and ask a doctor if irritation or rash occurs. These may be signs of a serious condition.

Keep out of reach of children. If swallowed, get medical help or contact a poison center immediately.

Other information

- Avoid freezing and excessive heat above 40C (104F)

Inactive ingredients

glycerin, hydrogen peroxide, purified water

Use

Hand sanitizer to help reduce disease-causing bacteria.

DOSAGE AND ADMINISTRATION

Apply liberally to dry hands, rub briskly until evaporated.
Children should be supervised when using this product.

Package Label - Principal Display Panel

80% ALCOHOL ANTISEPTIC TOPICAL SOLUTION

Antiseptic Hand Rub Non-Sterile Solution

12 oz | 355 mL

80% Alcohol v/v